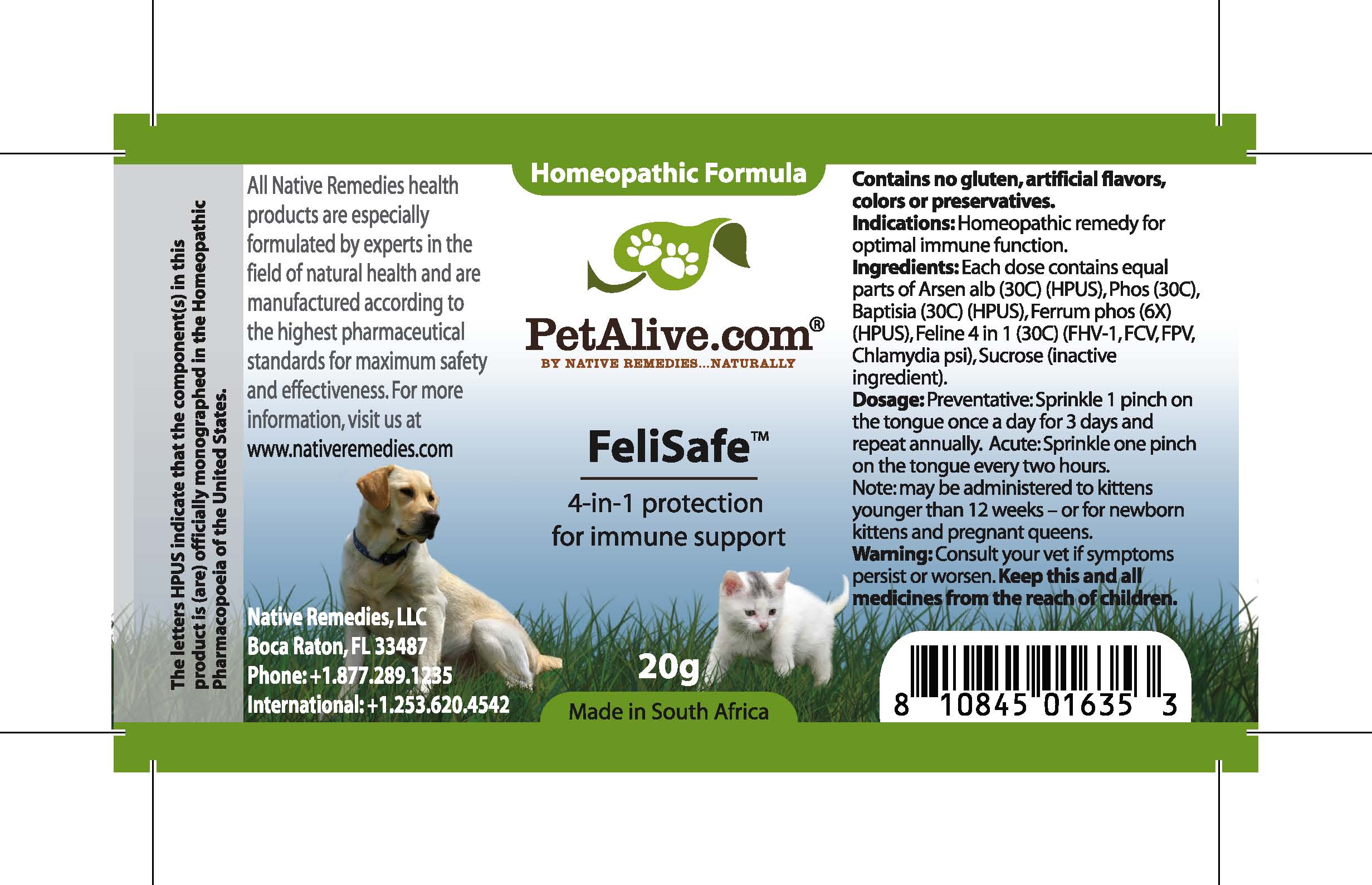 DRUG LABEL: Felisafe
NDC: 68647-105 | Form: GRANULE
Manufacturer: Feelgood Health
Category: homeopathic | Type: OTC ANIMAL DRUG LABEL
Date: 20100915

ACTIVE INGREDIENTS: ARSENIC TRIOXIDE 30 [hp_C]/50 mg; PHOSPHORUS 30 [hp_C]/50 mg; BAPTISIA 30 [hp_C]/50 mg; FERRUM PHOSPHORICUM 6 [hp_X]/50 mg
INACTIVE INGREDIENTS: SUCROSE 20000 mg/20000 mg

FELISAFE

PURPOSE

4-in-1 protection for immune support

Indications: Homeopathic remedy for optimal immune function.

DOSAGE AND ADMINISTRATION

Dosage: Preventative: Sprinkle 1 pinch on the tongue once a day for 3 days and repeat annually. Acute: Sprinkle one pinch on the tongue every two hours. May be administered to kittens younger than 12 weeks – or for newborn kittens and pregnant queens.

GENERAL PRECAUTIONS

Caution: Consult your vet if symptoms persist or worsen. Keep this and all medicines from the reach of children.

ACTIVE INGREDIENT

Ingredients: Each dose contains equal parts of Arsen alb (30C) (HPUS), Phos (30C), Baptisia (30C) (HPUS), Ferrum phos

Sucrose (inactive ingredient).

WARNINGS

Contains no gluten, artificial flavors, colors or preservatives.

PATIENT COUNSELING INFORMATION

All Native Remedies health products are especially formulated by experts in the field of natural health and are manufactured according to the highest pharmaceutical standards for maximum safety and effectiveness. For more information, visit us at www.petalive.com

Distributed by

Native Remedies, LLC

6531 Park of Commerce Blvd.

Suite 160

Boca Raton, FL 33487

Phone: 1.877.289.1235

International: + 1.561.999.8857

The letters HPUS indicate that the component(s) in this product is (are) officially monographed in the Homeopathic Pharmacopoeia of the United States.

KEEP OUT OF REACH OF CHILDREN

Keep this and all medicines from the reach of children.